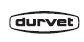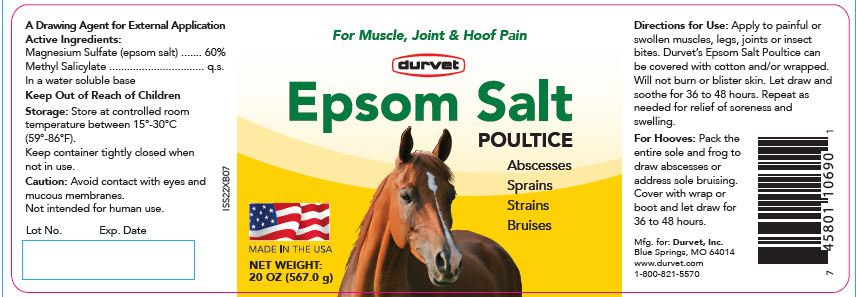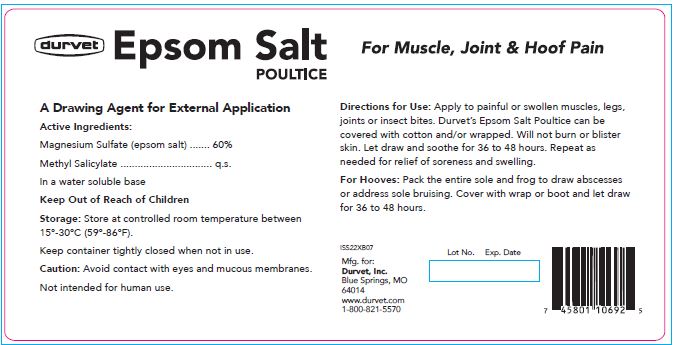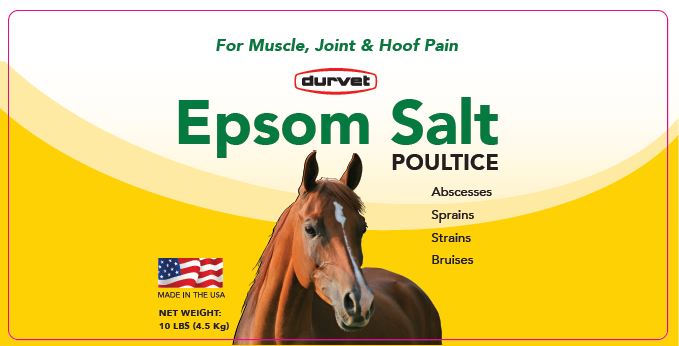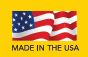 DRUG LABEL: Epsom Salt
NDC: 30798-929 | Form: POULTICE
Manufacturer: Durvet, Inc.
Category: animal | Type: OTC ANIMAL DRUG LABEL
Date: 20241029

ACTIVE INGREDIENTS: MAGNESIUM SULFATE HEPTAHYDRATE 600.5 mg/1 g; METHYL SALICYLATE 10 mg/1 g

Epsom Salt POULTICE

PURPOSE

For Muscle, Joint & Hoof Pain

Abscesses

Sprains

Strains

Bruises

NET WEIGHT:

20 OZ (567.0 g)

10 LBS (4.5 Kg)

VETERINARY INDICATIONS

A Drawing Agent for External Application

Active Ingredients:

Magnesium Sulfate (epsom salt) ....... 60%
Methyl Salicylate ................................ q.s.

INACTIVE INGREDIENT

In a water soluble base

Keep Out of Reach of Children

Storage:

Store at controlled room temperature between 15°-30°C (59°-86°F).

Keep container tightly closed when not in use.

Caution:

Avoid contact with eyes and mucous membranes.

Not intended for human use.

Directions for Use:

Apply to painful or swollen muscles, legs, joints or insect bites. Durvet's Epsom Salt Poultice can be covered with cotton and/or wrapped. Will not burn or blister skin. Let draw and soothe for 36 to 48 hours. Repeat as needed for relief of soreness and swelling.

For Hooves:

Pack the entire sole and frog to draw abscesses or address sole bruising. Cover with wrap or boot and let draw for 36 to 48 hours.

INFORMATION FOR OWNERS/CAREGIVERS

Mfg. for:
Durvet, Inc.
Blue Springs, MO 64014
www.durvet.com
1-800-821-5570